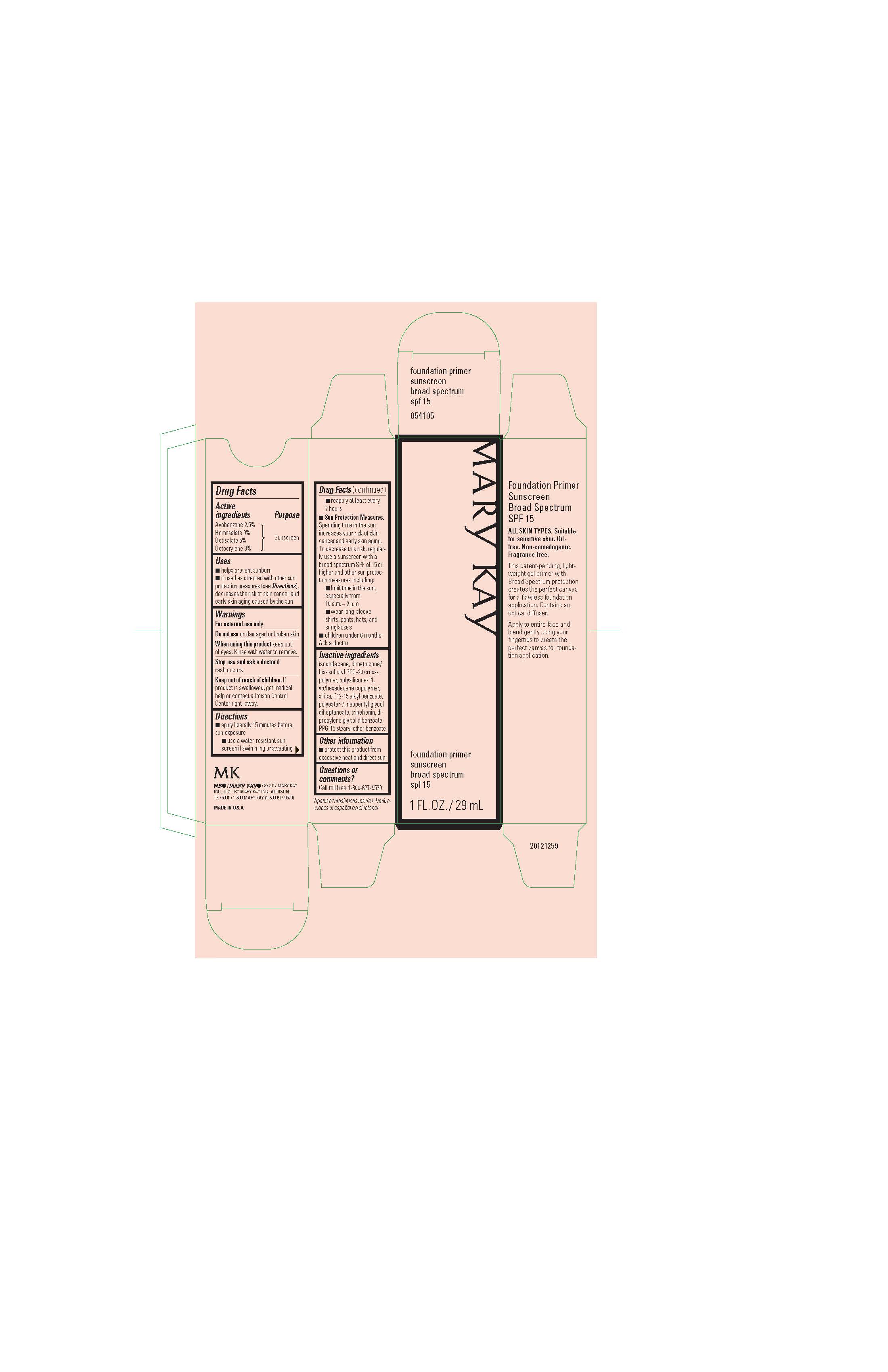 DRUG LABEL: Mary Kay Foundation Primer
NDC: 51531-0850 | Form: GEL
Manufacturer: Mary Kay Inc.
Category: otc | Type: HUMAN OTC DRUG LABEL
Date: 20241217

ACTIVE INGREDIENTS: AVOBENZONE 2.5 g/100 mL; HOMOSALATE 9 g/100 mL; OCTISALATE 5 g/100 mL; OCTOCRYLENE 3 g/100 mL
INACTIVE INGREDIENTS: DIMETHICONE/VINYL DIMETHICONE CROSSPOLYMER (SOFT PARTICLE); ISODODECANE; DIMETHICONE/BIS-ISOBUTYL PPG-20 CROSSPOLYMER; VINYLPYRROLIDONE/HEXADECENE COPOLYMER; SILICON DIOXIDE; ALKYL (C12-15) BENZOATE; POLYESTER-7; NEOPENTYL GLYCOL DIHEPTANOATE; TRIBEHENIN; DIPROPYLENE GLYCOL DIBENZOATE; PPG-15 STEARYL ETHER BENZOATE

Mary Kay Foundation Primer SPF 15
Drug Facts

Active Ingredients

Avobenzone 2.5%

Homosalate 9%

Octisalate 5%

Octocrylene 3%

Purpose

Sunscreen

Uses

- helps prevent sunburn
- if used as directed with other sun protection measures (see Directions), decreases the risk of skin cancer and early skin aging caused by the sun

Warnings

For external use only

Do not use

on damaged or broken skin

When using this product

keep out of eyes. Rinse with water to remove.

Stop use and ask a doctor

if rash occurs

Keep out of reach of children.

If product is swallowed, get medical help or contact a Poison Control Center right away.

Directions

- apply liberally 15 minutes before sun exposure
- use a water-resistant sunscreen if swimming or sweating
- reapply at least every 2 hours
- Sun Protection Measures. Spending time in the sun increases your risk of skin cancer and early skin aging. To decrease this risk, regularly use a sunscreen with a broad spectrum SPF of 15 or higher and other sun protection measures including:
- limit time in the sun, especially from 10 a.m. - 2 p.m.
- wear long-sleeve shirts, pants, hats, and sunglasses
- children under 6 months: Ask a doctor

Inactive ingredients

isododecane, dimethicone/bis-isobutyl PPG-20 crosspolymer, polysilicone-11, vp/hexadecene copolymer, silica, C12-15 alkyl benzoate, polyester-7, neopentyl glycol diheptanoate, tribehenin, dipropylene glycol dibenzoate, PPG-15 stearyl ether benzoate

Other information

protect this product from excessive heat and direct sun

Questions or comments?

Call toll free 1-800-627-9529

Principal Display Panel - 29 mL carton

Mary Kay

foundation primer

sunscreen

broad spectrum

spf 15

1 FL. OZ. / 29 mL